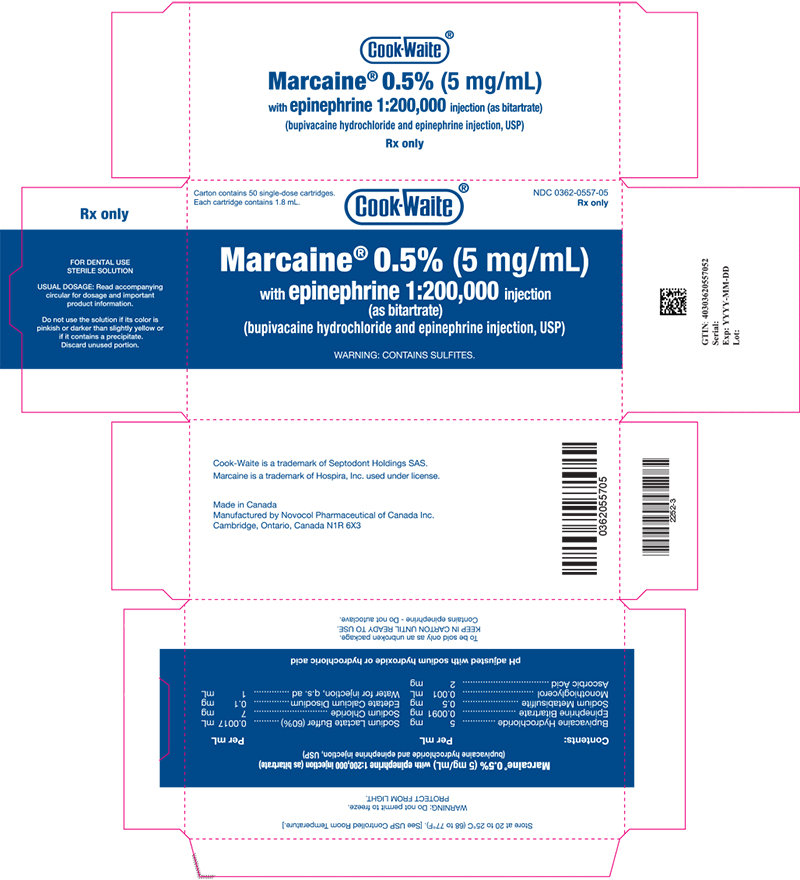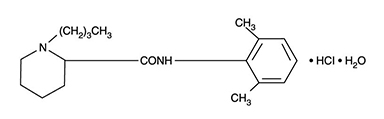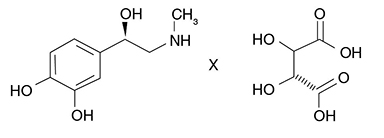 DRUG LABEL: Marcaine
NDC: 0362-0557 | Form: INJECTION, SOLUTION
Manufacturer: Septodont, Inc.
Category: prescription | Type: HUMAN PRESCRIPTION DRUG LABEL
Date: 20251010

ACTIVE INGREDIENTS: BUPIVACAINE HYDROCHLORIDE ANHYDROUS 5 mg/1 mL; epinephrine bitartrate 0.005 mg/1 mL
INACTIVE INGREDIENTS: sodium metabisulfite 0.5 mg/1 mL; sodium chloride 7 mg/1 mL; monothioglycerol 0.001 mL/1 mL; ascorbic acid 2 mg/1 mL; sodium lactate 0.0017 mL/1 mL; edetate calcium disodium 0.1 mg/1 mL; SODIUM HYDROXIDE; HYDROCHLORIC ACID; Water

Marcaine® 0.5% (5 mg/mL) with epinephrine 1:200,000 injection (as bitartrate)
(bupivacaine hydrochloride and epinephrine injection, USP)

Rx only

THIS SOLUTION IS INTENDED FOR DENTAL USE.

Description

Bupivacaine hydrochloride is (±) -1-Butyl-2´, 6´-pipecoloxylidide monohydrochloride, monohydrate, a white crystalline powder that is freely soluble in 95 percent ethanol, soluble in water, and slightly soluble in chloroform or acetone. It has the following structural formula:

Molecular Weight - 342.90 C18H28N2O • HCl • H2O

Epinephrine bitartrate is (-)-1-(3,4-Dihydroxyphenyl)-2-methylamino-ethanol (+) tartrate (1:1) salt. It has the following structural formula:

Molecular Weight - 333.29 C13H19NO9

Bupivacaine is available in a sterile isotonic solution with epinephrine 1:200,000 (as bitartrate). Solutions of bupivacaine containing epinephrine may not be autoclaved.
Bupivacaine is related chemically and pharmacologically to the aminoacyl local anesthetics. It is a homologue of mepivacaine and is chemically related to lidocaine. All three of these anesthetics contain an amide linkage between the aromatic nucleus and the amino or piperidine group. They differ in this respect from the procaine-type local anesthetics, which have an ester linkage.

CLINICAL PHARMACOLOGY

Bupivacaine stabilizes the neuronal membrane and prevents the initiation and transmission of nerve impulses, thereby effecting local anesthesia.

The onset of action following dental injections is usually 2 to 10 minutes and anesthesia may last two or three times longer than lidocaine and mepivacaine for dental use, in many patients up to 7 hours. The duration of anesthetic effect is prolonged by the addition of epinephrine 1:200,000.

It has also been noted that there is a period of analgesia that persists after the return of sensation, during which time the need for strong analgesic is reduced.

After injection of bupivacaine for caudal, epidural or peripheral nerve block in man, peak levels of bupivacaine in the blood are reached in 30 to 45 minutes, followed by a decline to insignificant levels during the next three to six hours. Because of its amide structure, bupivacaine is not detoxified by plasma esterases but is detoxified, via conjugation with glucuronic acid, in the liver. When administered in recommended doses and concentrations, bupivacaine does not ordinarily produce irritation or tissue damage.

Systemic absorption of local anesthetics produces effects on the cardiovascular and central nervous systems (CNS). At blood concentrations achieved with normal therapeutic doses, changes in cadiac conduction, excitability, refractoriness, contractility, and peripheral vascular resistance are minimal. However, toxic blood concentrations depress cardiac conduction and excitability, which may lead to atrioventricular block, ventricular arrhythmias, and cardiac arrest, sometimes resulting in fatalities. In addition, myocardial contractility is depressed and peripheral vasodilation occurs, leading to decreased cardiac output and arterial blood pressure. Recent clinical reports and animal research suggest that these cardiovascular changes are more likely to occur after unintended intravascular injection of bupivacaine. Therefore, incremental dosing is necessary.

Following systemic absorption, local anesthetics can produce central nervous system stimulation, depression, or both. Apparent central stimulation is manifested as restlessness, tremors and shivering progressing to convulsions, followed by depression and coma progressing ultimately to respiratory arrest. However, the local anesthetics have a primary depressant effect on the medulla and on higher centers. The depressed stage may occur without a prior excited state.

INDICATIONS AND USAGE

Marcaine® 0.5% (5 mg/mL) with epinephrine 1:200,000 injection is indicated for the production of local anesthesia for dental procedures by infiltration injection or nerve block in adults.
Marcaine® 0.5% (5 mg/mL) with epinephrine 1:200,000 injection is not recommended for children.

CONTRAINDICATIONS

Marcaine® 0.5% (5 mg/mL) with epinephrine 1:200,000 injection, is contraindicated in patients with a known hypersensitivity to it or to any local anesthetic agent of the amide type or to other components of bupivacaine solutions.

WARNINGS

LOCAL ANESTHETICS SHOULD BE EMPLOYED ONLY BY CLINICIANS WHO ARE WELL VERSED IN DIAGNOSIS AND MANAGEMENT OF DOSE-RELATED TOXICITY AND OTHER ACUTE EMERGENCIES WHICH MIGHT ARISE FROM THE BLOCK TO BE EMPLOYED, AND THEN ONLY AFTER INSURING THE IMMEDIATE AVAILABILITY OF OXYGEN, OTHER RESUSCITATIVE DRUGS, CARDIOPULMONARY RESUSCITATIVE EQUIPMENT, AND THE PERSONNEL RESOURCES NEEDED FOR PROPER MANAGEMENT OF TOXIC REACTIONS AND RELATED EMERGENCIES. (See also ADVERSE REACTIONS and PRECAUTIONS.) DELAY IN PROPER MANAGEMENT OF DOSE-RELATED TOXICITY, UNDERVENTILATION FROM ANY CAUSE, AND/OR ALTERED SENSITIVITY MAY LEAD TO THE DEVELOPMENT OF ACIDOSIS, CARDIAC ARREST AND, POSSIBLY, DEATH.

Small doses of local anesthetics injected into the head and neck area, as small as nine to eighteen milligrams, may produce adverse reactions similar to systemic toxicity seen with unintentional intravascular injections of larger doses. Confusion, convulsions, respiratory depression, and/or respiratory arrest, cardiovascular stimulation or depression and cardiac arrest have been reported. Reactions resulting in fatalities have occurred on rare occasions. In a few cases, resuscitation has been difficult or impossible despite apparently adequate preparation and appropriate management. These reactions may be due to intra-arterial injection of the local anesthetic with retrograde flow to the cerebral circulation. Patients receiving these blocks should have their circulation and respiration monitored and be constantly observed. Resuscitative equipment and personnel for treating adverse reactions should be immediately available. Dosage recommendations should not be exceeded (see DOSAGE AND ADMINISTRATION).

It is essential that aspiration for blood or cerebrospinal fluid (where applicable) be done prior to injecting any local anesthetic, both the original dose and all subsequent doses, to avoid intravascular injection. However, a negative aspiration does not ensure against an intravascular injection.

Reactions resulting in fatality have occurred on rare occasions with the use of local anesthetics, even in the absence of a history of hypersensitivity.

This solution, which contains a vasoconstrictor, should be used with extreme caution for patients whose medical history and physical evaluation suggest the existence of hypertension, arteriosclerotic heart disease, cerebral vascular insufficiency, heart block, thyrotoxicosis and diabetes, etc., as well as patients receiving drugs likely to produce alterations in blood pressure.

Methemoglobinemia: Cases of methemoglobinemia have been reported in association with local anesthetic use. Although all patients are at risk for methemoglobinemia, patients with glucose-6-phosphate dehydrogenase deficiency, congenital or idiopathic methemoglobinemia, cardiac or pulmonary compromise, infants under 6 months of age, and concurrent exposure to oxidizing agents or their metabolites more susceptible to developing clinical manifestations of the condition. If local anesthetics must be used in these patients, close monitoring for symptoms and signs of methemoglobinemia is recommended.

Signs of methemoglobinemia may occur immediately or may be delayed some hours after exposure, and are characterized by a cyanotic skin discoloration and/or abnormal coloration of the blood. Methemoglobin levels may continue to rise; therefore, immediate treatment is required to avert more serious central nervous system and cardiovascular adverse effects, including seizures, coma, arrhythmias, and death. Discontinue Marcaine® and any other oxidizing agents. Depending on the severity of the signs and symptoms, patients may respond to supportive care, i.e., oxygen therapy, hydration. A more severe clinical presentation may require treatment with methylene
blue, exchange transfusion, or hyperbaric oxygen.

Marcaine® 0.5% (5 mg/mL) with epinephrine 1:200,000 injection or other vasopressors should not be used concomitantly with ergot-type oxytocic drugs, because a severe persistent hypertension may occur. Likewise, solutions of bupivacaine containing a vasoconstrictor, such as epinephrine, should be used with extreme caution in patients receiving monoamine oxidase inhibitors (MAOI) or antidepressants of the triptyline or imipramine types, because severe prolonged hypertension may result.

Until further experience is gained in children younger than 12 years, administration of bupivacaine in this age group is not recommended.

Contains sodium metabisulfite, a sulfite that may cause allergic-type reactions including anaphylactic symptoms and life-threatening or less severe asthmatic episodes in certain susceptible people. The overall prevalence of sulfite sensitivity in the general population is unknown and probably low. Sulfite sensitivity is seen more frequently in asthmatic than in nonasthmatic people.

PRECAUTIONS

The safety and effectiveness of local anesthetics depend upon proper dosage, correct technique, adequate precautions, and readiness for emergencies.

The lowest dosage that gives effective anesthesia should be used in order to avoid high plasma levels and serious systemic side effects. Injection of repeated doses of bupivacaine may cause significant increase in blood levels with each additional dose, due to accumulation of the drug or its metabolites or due to slow metabolic degradation. Tolerance varies with the status of the patient.

Debilitated, elderly patients and acutely ill patients should be given reduced doses commensurate with age and physical condition.

Because of the long duration of anesthesia, when bupivacaine with epinephrine is used for dental injections, patients should be cautioned about the possibility of inadvertent trauma to tongue, lips, and buccal mucosa and advised not to chew solid foods or test the anesthetized area by biting or probing.

Changes in sensorium, such as excitation, disorientation, drowsiness, may be early indications of a high blood level of the drug and may occur following inadvertent intravascular administration or rapid absorption of bupivacaine.

Solutions containing a vasoconstrictor should be used cautiously in areas with limited blood supply, in the presence of diseases that may adversely affect the patient's cardiovascular system, or in patients with peripheral vascular disease.

Caution is advised in administration of repeat doses of bupivacaine to patients with severe liver disease.

Local anesthetic procedures should be used with caution when there is inflammation and/or sepsis in the region of the proposed injection.

Drug Interactions

See WARNINGS concerning solutions containing a vasoconstrictor.

If sedatives are employed to reduce patient apprehension, use reduced doses, since local anesthetic agents, like sedatives, are central nervous system depressants which in combination may have an additive effect.

Marcaine® 0.5% (5 mg/mL) with epinephrine 1:200,000 injection should be used cautiously in persons with known drug allergies or sensitivities, particularly to the amide-type local anesthetics. Serious dose-related cardiac arrhythmias may occur if preparations containing a vasoconstrictor such as epinephrine are employed in patients during or following the administration of chloroform, halothane, cyclopropane, trichloroethylene, or other related agents. In deciding whether to use these products concurrently in the same patient, the combined action of both agents upon the myocardium, the concentration and volume of vasoconstrictor used, and the time since injection, when applicable, should be taken into account.

Information for Patients/Patient Counseling Information

When appropriate, the dentist should discuss information including adverse reactions in the package insert for Marcaine® 0.5% (5 mg/mL) with epinephrine 1:200,000 injection. Inform patients that use of local anesthetics may cause methemoglobinemia, a serious condition that must be treated promptly. Advise patients or caregivers to seek immediate medical attention if they or someone in their care experience the following signs or symptoms: pale, gray, or blue colored skin (cyanosis); headache; rapid heart rate; shortness of breath; lightheadedness; or fatigue.

Clinically Significant Drug Interactions

The administration of local anesthetic solutions containing epinephrine or norepinephrine to patients receiving mono-amine oxidase inhibitors or tricyclic antidepressants may produce severe, prolonged hypertension. Concurrent use of these agents should generally be avoided. In situations when concurrent therapy is necessary, careful patient monitoring is essential.

Concurrent administration of vasopressor drugs and of ergot-type oxytocic drugs may cause severe, persistent hypertension or cerebrovascular accidents.

Phenothiazines and butyrophenones may reduce or reverse the pressor effect of epinephrine.

Patients who are administered local anesthetics are at increased risk of developing methemoglobinemia when concurrently exposed to the following drugs, which could include other local anesthetics:

EXAMPLES OF DRUGS ASSOCIATED WITH METHEMOGLOBINEMIA:
Class | Examples
Nitrates/Nitrites | nitric oxide, nitroglycerin, nitroprusside, nitrous oxide
Local anesthetics | articaine, benzocaine, bupivacaine, lidocaine, mepivacaine, prilocaine, procaine, ropivacaine, tetracaine
Antineoplastic Agents | cyclophosphamide, flutamide, hydroxyurea, ifosfamide, rasburicase
Antibiotics | dapsone, nitrofurantoin, para-aminosalicylic acid, sulfonamides
Antimalarials | chloroquine, primaquine
Anticonvulsants | phenobarbital, phenytoin, sodium valproate
Other drugs | acetaminophen, metoclopramide, quinine, sulfasalazine

Carcinogenesis, Mutagenesis, Impairment of Fertility

Long-term studies in animals to evaluate the carcinogenic potential of bupivacaine hydrochloride have not been conducted. The mutagenic potential and the effect on fertility of bupivacaine hydrochloride has not been determined.

Pregnancy Category C

TERATOGENIC EFFECTS

There are no adequate and well-controlled studies in pregnant women. Bupivacaine should be used during pregnancy only if the potential benefit justifies the potential risk to the fetus. Bupivacaine hydrochloride produced development toxicity when administered subcutaneously to pregnant rats and rabbits at clinically relevant doses. This does not exclude the use of bupivacaine at term for obstetrical anesthesia or analgesia.

Bupivacaine hydrochloride was administered subcutaneously to rats at doses of 4.4, 13.3, and 40 mg/kg and to rabbits at doses of 1.3, 5.8, and 22.2 mg/kg during the period of organogenesis (implantation to closure of the hard palate). The high doses are approximately 4-times the daily maximum recommended human dose (MRHD) of 90 mg/day on a mg dose/m2 body surface area (BSA) basis. No embryo-fetal effects were observed in rats at the high dose which caused increased maternal lethality. An increase in embryo-fetal deaths was observed in rabbits at the high dose in the absence of maternal toxicity with the fetal No Observed Adverse Effect Level being a comparable dose to the MRHD on a BSA basis.

In a rat pre- and post-natal development study (dosing from implantation through weaning) conducted at subcutaneous doses of 4.4, 13.3 and 40 mg/kg mg/kg/day, decreased pup survival was observed at the high dose. The high dose is approximately 4-time the daily MRHD of 90 mg/day on a BSA basis.

Nursing Mothers

It is not known whether local anesthetic drugs are excreted in human milk. Because many drugs are excreted in human milk, caution should be exercised when local anesthetics are administered to a nursing woman.

Pediatric Use

Until further experience is gained in children younger than 12 years, administration of bupivacaine in this age group is not recommended.

ADVERSE REACTIONS

Reactions to Marcaine® 0.5% (5 mg/mL) with epinephrine 1:200,000 injection are characteristic of those associated with other amide-type local anesthetics. A major cause of adverse reactions to this group of drugs is excessive plasma levels, which may be due to overdosage, inadvertent intravascular injection or slow metabolic degradation.

Excessive plasma levels of the amide-type local anesthetics cause systemic reactions involving the central nervous system and the cardiovascular system. The central nervous system effects are characterized by excitation or depression. The first manifestation may be nervousness, dizziness, blurred vision, or tremors, followed by drowsiness, convulsions, unconsciousness, and possibly respiratory arrest. Since excitement may be transient or absent, the first manifestation may be drowsiness, sometimes merging into unconsciousness and respiratory arrest. Other central nervous system effects may be nausea, vomiting, chills, constriction of the pupils, or tinnitus. The cardiovascular manifestations of excessive plasma levels may include depression of the myocardium, blood pressure changes (usually hypotension), and cardiac arrest. Allergic reactions, which may be due to hypersensitivity, idiosyncrasy, or diminished tolerance, are characterized by cutaneous lesions (e.g., urticaria), edema, and other manifestations of allergy. Detection of sensitivity by skin testing is of doubtful value. Transient facial swelling and puffiness may occur near the injection site.

Treatment of Reactions

Toxic effects of local anesthetics require symptomatic treatment; there is no specific cure. The dentist should be prepared to maintain an airway and to support ventilation with oxygen and assisted or controlled respiration as required. Supportive treatment of the cardiovascular system includes intravenous fluids and, when appropriate, vasopressors (preferably those that stimulate the myocardium). Convulsions may be controlled with oxygen and intravenous administration, in small increments, of a barbiturate, as follows: preferably, an ultra-short-acting barbiturate such as thiopental or thiamylal; if this is not available, a short-acting barbiturate (e.g., secobarbital or pentobarbital) or diazepam. Intravenous barbiturates or anticonvulsant agents should only be administered by those familiar with their use.

DOSAGE AND ADMINISTRATION

As with all anesthetics, the dosage varies and depends upon the area to be anesthetized, the vascularity of the tissues, the number of neuronal segments to be blocked, individual tolerance, and the technique of anesthesia. The lowest dosage needed to provide effective anesthesia should be administered. For specific techniques and procedures, refer to standard textbooks.

The 0.5% concentration with epinephrine is recommended for infiltration and block injection in the maxillary and mandibular area when a longer duration of local anesthetic action is desired, such as for oral surgical procedures generally associated with significant postoperative pain. The average dose of 1.8 mL (9 mg) per injection site will usually suffice; an occasional second dose of 1.8 mL (9 mg) may be used if necessary to produce adequate anesthesia after making allowance for 2 to 10 minutes onset time (see CLINICAL PHARMACOLOGY). The lowest effective dose should be employed and time should be allowed between injections; it is recommended that the total dose for all injection sites, spread out over a single dental sitting, should not ordinarily exceed 90 mg for a healthy adult patient (ten 1.8 mL injections of bupivacaine with epinephrine). Injections should be made slowly and with frequent aspirations. Until further experience is gained, bupivacaine in dentistry is not recommended for children younger than 12 years.

Parental drug products should be inspected visually for particulate matter and discoloration prior to administration, whenever solution and container permit. Discard unused portion.

HOW SUPPLIED

STORAGE AND HANDLING

Store at 20 to 25°C (68 to 77°F). [See USP Controlled Room Temperature.] Protect from light. Do not permit to freeze.

Marcaine® 0.5% (5 mg/mL) with epinephrine 1:200,000 injection, (as bitartrate)–Sterile isotonic solutions containing sodium chloride. Each 1 mL contains 5 mg bupivacaine hydrochloride and 0.0091 mg epinephrine bitartrate, with 0.5 mg sodium metabisulfite, 7 mg sodium chloride, 0.001 mL monothioglycerol, and 2 mg ascorbic acid as antioxidants, 0.0017 mL 60% sodium lactate buffer, and 0.1 mg edetate calcium disodium as stabilizer. The pH of these solutions is adjusted with sodium hydroxide or hydrochloric acid. Solutions of bupivacaine that contain epinephrine should not be autoclaved and should be protected from light. Do not use the solution if its colour is pinkish or darker than slightly yellow or if it contains a precipitate.

Marcaine® 0.5% (5 mg/mL) with epinephrine 1:200,000 injection (NDC 0362-0557-05) is available in cartons containing 5 blisters of 10 X 1.8 mL single-dose dental cartridges.

Manufactured by

Novocol Pharmaceutical of Canada Inc.

Cambridge, Ontario, Canada N1R 6X3

Rev. 02/2020 (2269-2)

Cook-Waite is a trademark of Septodont Holdings SAS

PRINCIPAL DISPLAY PANEL - 1.8 mL Cartridge Carton

Carton contains 50 single-dose cartridges.

Each cartridge contains 1.8 mL.

Cook-Waite®

NDC 0362-0557-05

Rx only

Marcaine® 0.5% (5 mg/mL) with epinephrine 1:200,000 injection (as bitartrate)
(bupivacaine hydrochloride and epinephrine Injection, USP)

WARNINGS: CONTAINS SULFITES